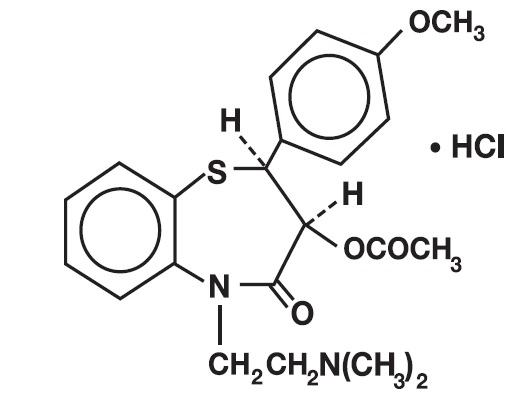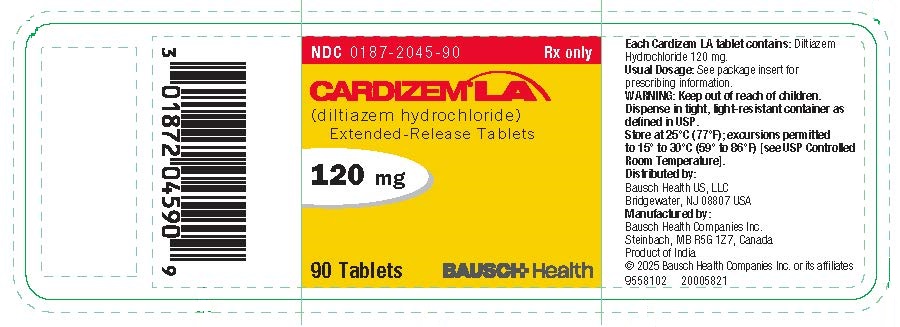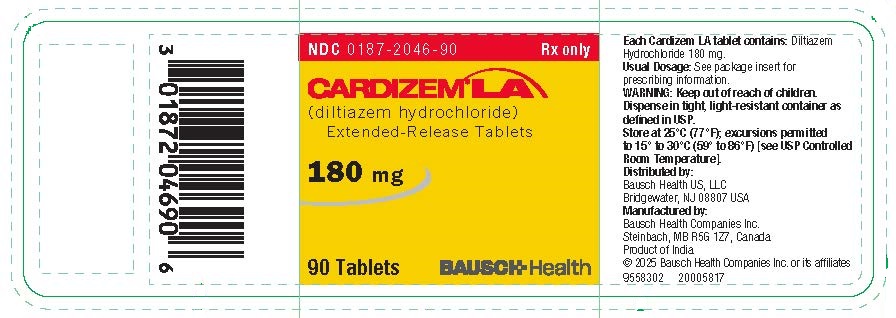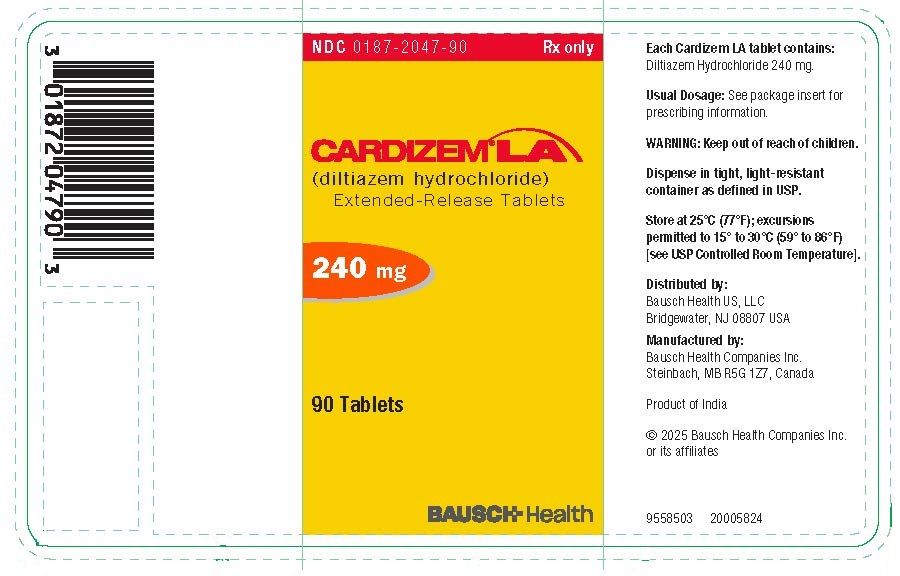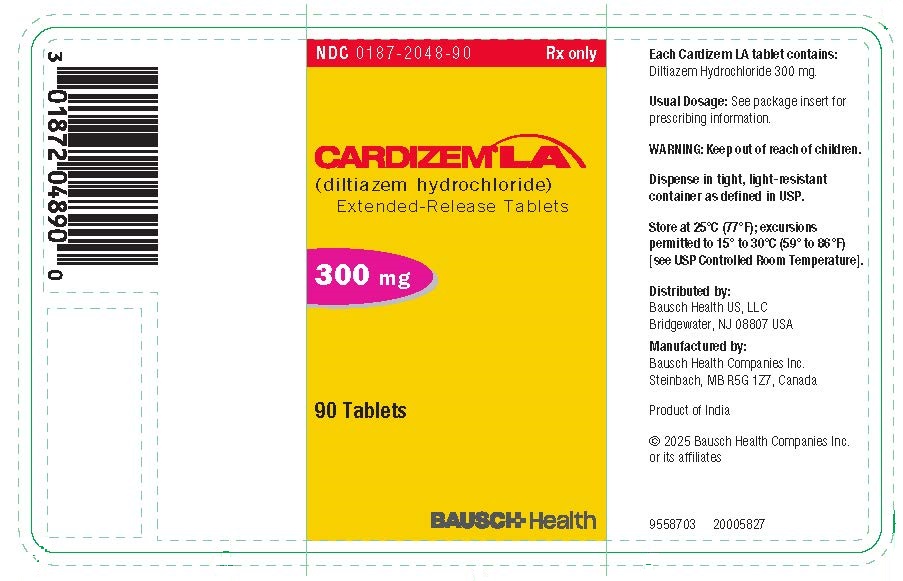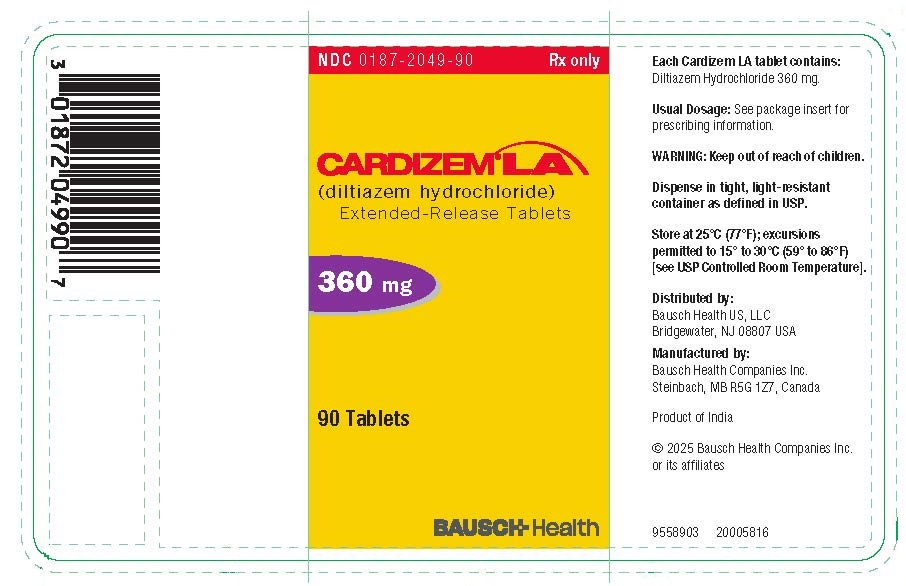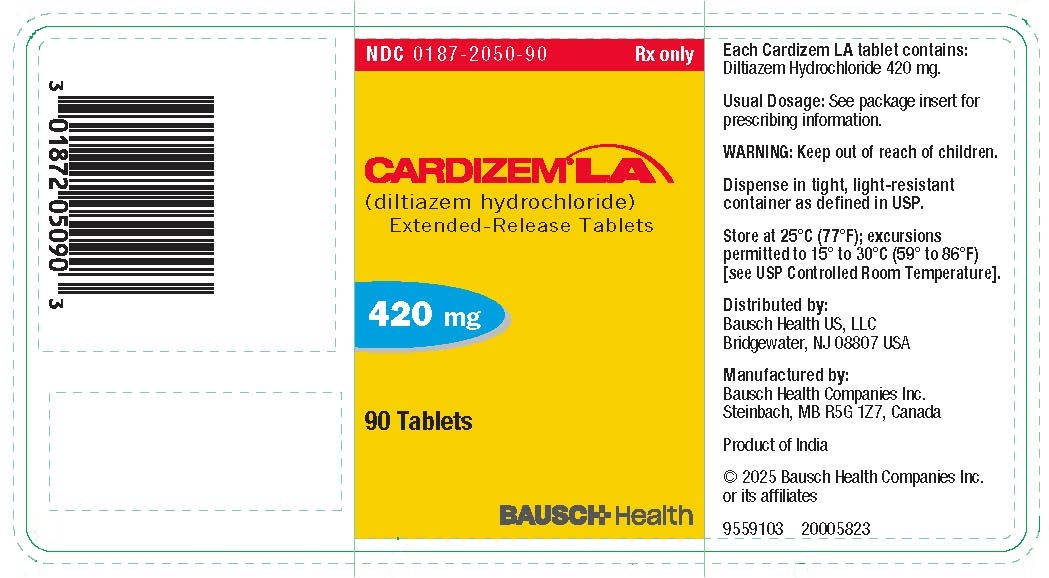 DRUG LABEL: Cardizem LA
NDC: 0187-2045 | Form: TABLET, EXTENDED RELEASE
Manufacturer: Bausch Health US LLC
Category: prescription | Type: HUMAN PRESCRIPTION DRUG LABEL
Date: 20251111

ACTIVE INGREDIENTS: DILTIAZEM HYDROCHLORIDE 120 mg/1 1
INACTIVE INGREDIENTS: CARNAUBA WAX; SILICON DIOXIDE; CROSCARMELLOSE SODIUM; ETHYL ACRYLATE AND METHYL METHACRYLATE COPOLYMER (2:1; 750000 MW); HYPROMELLOSE, UNSPECIFIED; MAGNESIUM STEARATE; MICROCRYSTALLINE CELLULOSE; MICROCRYSTALLINE WAX; POLYDEXTROSE; POLYETHYLENE GLYCOL, UNSPECIFIED; POLYSORBATE 80; POVIDONE, UNSPECIFIED; SUCROSE STEARATE; TALC; TITANIUM DIOXIDE

HIGHLIGHTS OF PRESCRIBING INFORMATION

These highlights do not include all the information needed to use CARDIZEM LA safely and effectively. See full prescribing information for CARDIZEM LA.
CARDIZEM® LA (diltiazem hydrochloride) extended-release tablets, for oral use
Initial U.S. Approval: 1982

1 INDICATIONS AND USAGE

CARDIZEM LA is a nondihydropyridine calcium channel blocker indicated for:

- treatment of hypertension, to lower blood pressure. Lowering blood pressure reduces the risk of fatal and nonfatal cardiovascular events, primarily strokes and myocardial infarctions. It can be used alone or in combination with other antihypertensives. (1.1)
- improving exercise tolerance in patients with chronic stable angina. (1.2)

2 DOSAGE AND ADMINISTRATION

- Tablet should be swallowed whole and not chewed or crushed. (2)
- Hypertension: Initial adult dose is 180 to 240 mg once daily. Adjust dose according to blood pressure response to a maximum of 540 mg daily. (2.1)
- Angina: Initial adult dose is 180 mg once daily. Adjust dose according to response to a maximum of 360 mg. (2.2)
- Switching to CARDIZEM LA: Patients may be switched to the nearest equivalent total daily diltiazem dose. (2.3)

3 DOSAGE FORMS AND STRENGTHS

- Extended-release tablets with 120 mg, 180 mg, 240 mg, 300 mg, 360 mg, or 420 mg diltiazem hydrochloride per tablet. (3)

4 CONTRAINDICATIONS

- Sick sinus syndrome except in the presence of a functioning ventricular pacemaker. (4)
- Second- or third-degree AV block except in the presence of a functioning ventricular pacemaker. (4)
- Hypotension (less than 90 mm Hg systolic). (4)
- Hypersensitivity to the drug. (4)
- Acute myocardial infarction and pulmonary. (4)

5 WARNINGS AND PRECAUTIONS

- Bradycardia, second- or third-degree AV block: Monitor heart rate and rhythm. (5.1)
- Heart failure: Monitor for signs and symptoms. (5.2)
- Increased liver enzymes and acute hepatic injury. (5.3)
- Severe skin reactions. (5.4)

6 ADVERSE REACTIONS

The most common adverse reactions (>2%) are lower limb edema, sinus congestion and rash in patients treated for hypertension, and lower limb edema, headache, dizziness, fatigue, bradycardia, first-degree AV block and cough in patients treated for angina. (6.1)

To report SUSPECTED ADVERSE REACTIONS, contact Bausch Health US, LLC at 1-800-321-4576 or FDA at 1-800-FDA-1088 or www.fda.gov/medwatch.

7 DRUG INTERACTIONS

- Beta-blockers, digitalis, and other agents known to impair cardiac contractility and conduction may increase risk for hypotension, bradycardia, and heart failure. (7.1)
- CYP450 3A4: Diltiazem is both a substrate and inhibitor of CYP450 3A4. CYP450 3A4 substrates may require dosage adjustment. (7.2)

FULL PRESCRIBING INFORMATION

1 INDICATIONS AND USAGE

1.1 Hypertension

CARDIZEM® LA is indicated for the treatment of hypertension, to lower blood pressure. Lowering blood pressure reduces the risk of fatal and nonfatal cardiovascular events, primarily strokes and myocardial infarctions. These benefits have been seen in controlled trials of antihypertensive drugs from a wide variety of pharmacologic classes including this drug.

Control of high blood pressure should be part of comprehensive cardiovascular risk management, including, as appropriate, lipid control, diabetes management, antithrombotic therapy, smoking cessation, exercise, and limited sodium intake. Many patients will require more than one drug to achieve blood pressure goals. For specific advice on goals and management, see published guidelines, such as those of the National High Blood Pressure Education Program’s Joint National Committee on Prevention, Detection, Evaluation, and Treatment of High Blood Pressure (JNC).

Numerous antihypertensive drugs, from a variety of pharmacologic classes and with different mechanisms of action, have been shown in randomized controlled trials to reduce cardiovascular morbidity and mortality, and it can be concluded that it is blood pressure reduction, and not some other pharmacologic property of the drugs, that is largely responsible for those benefits. The largest and most consistent cardiovascular outcome benefit has been a reduction in the risk of stroke, but reductions in myocardial infarction and cardiovascular mortality also have been seen regularly.

Elevated systolic or diastolic pressure causes increased cardiovascular risk, and the absolute risk increase per mm Hg is greater at higher blood pressures, so that even modest reductions of severe hypertension can provide substantial benefit. Relative risk reduction from blood pressure reduction is similar across populations with varying absolute risk, so the absolute benefit is greater in patients who are at higher risk independent of their hypertension (for example, patients with diabetes or hyperlipidemia), and such patients would be expected to benefit from more aggressive treatment to a lower blood pressure goal.

Some antihypertensive drugs have smaller blood pressure effects (as monotherapy) in black patients, and many antihypertensive drugs have additional approved indications and effects (e.g., on angina, heart failure, or diabetic kidney disease). These considerations may guide selection of therapy.

CARDIZEM LA may be used alone or in combination with other antihypertensive medications.

1.2 Angina

CARDIZEM LA is indicated to improve exercise tolerance in patients with chronic stable angina.

2 DOSAGE AND ADMINISTRATION

Take CARDIZEM LA once a day at approximately the same time. Do not chew or crush the tablet.

2.1 Hypertension

Initiate dosing at 180 to 240 mg once daily, although some patients may respond to lower doses. Titrate according to blood pressure to a maximum of 540 mg daily. Maximum antihypertensive effect is usually observed by 14 days of chronic therapy.

2.2 Angina

Initiate dosing at 180 mg once daily and increase dose at intervals of 7 to 14 days if adequate response is not obtained, to a maximum of 360 mg.

2.3 Switching to CARDIZEM LA Tablets

Patients controlled on diltiazem alone or in combination with other medications may be switched to CARDIZEM LA once a day at the nearest equivalent total daily dose. Higher doses of CARDIZEM LA may be needed in some patients based on clinical response.

3 DOSAGE FORMS AND STRENGTHS

Extended-release tablets with 120 mg, 180 mg, 240 mg, 300 mg, 360 mg, or 420 mg diltiazem hydrochloride per tablet. CARDIZEM LA Tablets are supplied as capsule shaped, white film-coated tablets, debossed with “B” on one side and the diltiazem content (mg) on the other.

4 CONTRAINDICATIONS

CARDIZEM LA is contraindicated in:

- Patients with sick sinus syndrome except in the presence of a functioning ventricular pacemaker.
- Patients with second- or third-degree AV block except in the presence of a functioning ventricular pacemaker.
- Patients with hypotension (less than 90 mm Hg systolic).
- Patients who have demonstrated hypersensitivity to the drug.
- Patients with acute myocardial infarction and pulmonary.

5 WARNINGS AND PRECAUTIONS

5.1 Bradycardia or AV Block

CARDIZEM LA may cause abnormally slow heart rates or second- or third-degree AV block. Patients with sick sinus syndrome are at increased risk of bradycardia. Concomitant use of diltiazem with beta-blockers or digitalis may result in additive effects on cardiac conduction. A patient with Prinzmetal’s angina developed periods of asystole (2 to 5 seconds) after a single dose of 60 mg of diltiazem [see Adverse Reactions (6)]. Monitor for effects on heart rate and cardiac conduction.

5.2 Heart Failure

Worsening of heart failure has been reported in patients with impairment of ventricular function. Experience with the use of diltiazem in combination with beta-blockers in patients with impaired ventricular function is limited.

5.3 Acute Hepatic Injury

Significant elevations in liver enzymes such as alkaline phosphatase, LDH, AST (SGOT), ALT (SGPT) and signs of acute hepatic injury have been reported with diltiazem therapy. These reactions tended to occur early after therapy initiation (1 to 8 weeks) and have been reversible upon discontinuation of drug therapy. Mild elevations of transaminases with and without concomitant elevation in alkaline phosphatase and bilirubin have also been observed. Such elevations were usually transient and frequently resolved even with continued diltiazem treatment.

5.4 Severe Skin Reactions

Stevens-Johnson syndrome, toxic epidermal necrolysis, erythema multiforme and/or exfoliative dermatitis have been reported.

6 ADVERSE REACTIONS

The following adverse reactions are described in greater detail, in other sections:

- Bradycardia and AV block [see Warnings and Precautions (5.1)]
- Heart failure [see Warnings and Precautions (5.2)]
- Acute hepatic injury [see Warnings and Precautions (5.3)]
- Severe skin reactions [see Warnings and Precautions (5.4)]

6.1 Clinical Trials Experience

Because clinical trials are conducted under widely varying conditions, adverse reaction rates observed in the clinical trials of a drug cannot be directly compared to rates in the clinical trials of another drug and may not reflect the rates observed in practice.

For the hypertension studies, the following table presents adverse reactions more common on diltiazem than on placebo (but excluding events with no plausible relationship to treatment), as reported in placebo-controlled hypertension trials in patients receiving a diltiazem hydrochloride extended-release formulation (once-a-day dosing) up to 540 mg.

 | Placebo | Diltiazem hydrochloride extended-release
Adverse Reactions (MedDRA Term) | n=120 # pts. (%) | 120-360 mg n=501 # pts. (%) | 540 mg n=123 # pts. (%)
Edema lower limb | 4 (3) | 24 (5) | 10 (8)
Sinus congestion | 0 (0) | 2 (1) | 2 (2)
Rash | 0 (0) | 3 (1) | 2 (2)

In the angina study, the adverse event profile of CARDIZEM LA was consistent with what has been previously described for CARDIZEM LA and other formulations of diltiazem HCl. The most frequent adverse effects experienced by CARDIZEM LA-treated patients were edema lower-limb (6.8%), dizziness (6.4%), fatigue (4.8%), bradycardia (3.6%), first-degree atrioventricular block (3.2%), and cough (2%).

In addition, the following events have been reported infrequently (less than 1%) in angina or hypertension trials:

Cardiovascular: Angina, bundle branch block, palpitations, syncope, tachycardia, ventricular extrasystoles [see Warnings and Precautions (5.1, 5.2)].

Nervous System: Abnormal dreams, amnesia, depression, gait abnormality, hallucinations, insomnia, nervousness, paresthesia, personality change, somnolence, tinnitus, tremor.

Gastrointestinal: Anorexia, constipation, diarrhea, dry mouth, dysgeusia, dyspepsia, thirst, vomiting, weight increase.

Dermatological: Petechiae, photosensitivity, pruritus, urticaria [see Warnings and Precautions (5.4)].

Other: Amblyopia, CPK increase, dyspnea, epistaxis, eye irritation, hyperglycemia, hyperuricemia, impotence, muscle cramps, nasal congestion, nocturia, osteoarticular pain, polyuria, sexual difficulties.

6.2 Post-Marketing Experience

The following adverse reactions have been identified during post-approval use of diltiazem. Because these reactions are reported voluntarily from a population of uncertain size, it is not always possible to estimate their frequency or establish a causal relationship to drug exposure.

The following post-marketing reactions have been reported infrequently in patients receiving diltiazem: acute generalized exanthematous pustulosis, allergic reactions, alopecia, angioedema (including facial or periorbital edema), erythema multiforme, extrapyramidal symptoms, gingival hyperplasia, hemolytic anemia, increased bleeding time, leukopenia, photosensitivity (including lichenoid keratosis and hyperpigmentation at sun-exposed skin areas), purpura, retinopathy, myopathy, and thrombocytopenia.

In addition, events such as myocardial infarction have been observed which are not readily distinguishable from the natural history of the disease in these patients.

A number of well-documented cases of generalized rash, some characterized as leukocytoclastic vasculitis, have been reported.

7 DRUG INTERACTIONS

7.1 Agents Known to Impair Cardiac Contractility and Conduction

Using other agents known to affect cardiac conduction or contractility with diltiazem may increase the risk of bradycardia, AV block, and heart failure [see Warnings and Precautions (5.1, 5.2)].

Ivabradine: Concurrent use of diltiazem increases exposure to ivabradine and may exacerbate bradycardia and conduction disturbances. Avoid concomitant use of ivabradine and diltiazem.

7.2 P-glycoprotein (P-gp) and Cytochrome P450 3A4 Mediated Drug Interactions

Diltiazem is both a substrate and an inhibitor of the Pg-p and cytochrome P450 3A4 enzyme system which may affect exposure to diltiazem and concomitant drugs metabolized by those pathways. Patients with renal and/or hepatic impairment may be particularly at risk of exposure changes [see Clinical Pharmacology (12.3)].

8 USE IN SPECIFIC POPULATIONS

8.1 Pregnancy

Risk Summary

The available data from the published literature over decades of use with diltiazem during pregnancy have not identified a drug associated risk of major birth defects, miscarriage, or adverse maternal or fetal outcomes. In animal reproduction studies in rats and rabbits, administration of diltiazem to pregnant animals during organogenesis at oral doses approximately 1 and 4 times the Maximum Recommended Human Dose (MRHD) of CARDIZEM LA produced embryofetal deaths and increased incidence of skeletal abnormalities. An increased incidence of stillbirths was noted at diltiazem doses approximately 2 times the MRHD of CARDIZEM LA.

The estimated background risk of major birth defects and miscarriage for the indicated population is unknown. All pregnancies have a background risk of major birth defects, loss, and other adverse outcomes. In the U.S. general population, the estimated background risk of major birth defects and miscarriage in clinically recognized pregnancies is 2-4% and 15-20%, respectively.

Data

Animal Data

Embryofetal development studies have been conducted with diltiazem in rats and rabbits. Daily oral administration of diltiazem at 0, 17.5, 35 or 70 mg/kg to pregnant rabbits during organogenesis (gestational day 6 to 18) resulted in embryo-fetal lethality at 35 mg/kg/day (approximately 1 time the MRHD of CARDIZEM LA, on a mg/m2 basis) and higher, concurrent with maternal toxicity (reduced body weight gain). Daily oral administration of diltiazem at 0, 100, 200 and 400 mg/kg to pregnant rats during organogenesis (gestation day 9 to 14) resulted in embryo-fetal lethality at 200 mg/kg/day (approximately 4 times the MRHD of CARDIZEM LA, on a mg/m^2 basis) and higher. These doses, in some studies, were reported to cause increased incidence of skeletal malformations (e.g. malformations of vertebral column) or variations. In an oral perinatal/postnatal study in rats with diltiazem at 0, 50, 100, 200 and 400 mg/kg/day from gestation day 15 to lactation/post-partum day 20, there was an increased incidence of stillbirths at 100 mg/kg/day, approximately 2 times (on a mg/m^2 basis) the MRHD of CARDIZEM LA.

8.2 Lactation

Risk Summary

Diltiazem is excreted in human milk. One report suggests that concentrations in breast milk may approximate serum levels. Because of the potential for serious adverse reactions in nursing infants from diltiazem, a decision should be made whether to discontinue nursing or to discontinue the drug, taking into account the importance of the drug to the mother.

The developmental and health benefits of breastfeeding should be considered along with the mother's clinical need for diltiazem and any potential adverse effects on the breastfed child from diltiazem or from the underlying maternal condition.

8.4 Pediatric Use

Safety and effectiveness in pediatric patients have not been established.

8.5 Geriatric Use

Clinical studies of diltiazem did not include sufficient numbers of subjects aged 65 and over to determine whether they respond differently from younger subjects. Other reported clinical experience has not identified differences in responses between the elderly and younger patients. In general, dose selection for an elderly patient should be cautious, usually starting at the low end of the dosing range, reflecting the greater frequency of decreased hepatic, renal, or cardiac function, and of concomitant disease or other drug therapy.

8.6 Use in Renal Impairment

No dose adjustment is necessary.

8.7 Use in Hepatic Impairment

No dose adjustment is likely to be needed for mild-moderate hepatic impairment.

10 OVERDOSAGE

The oral LD50 is 415 to 740 mg/kg in mice and 560 to 810 mg/kg in rats. The intravenous LD50 is 60 mg/kg in mice and 38 mg/kg in rats. The oral LD50 in dogs is considered to be in excess of 50 mg/kg, while lethality was seen in monkeys at 360 mg/kg.

The toxic dose in man is not known. Blood levels after a standard dose of diltiazem can vary over tenfold, limiting the usefulness of blood levels in overdose cases.

There have been 29 reports of diltiazem overdose in doses ranging from less than 1 g to 18 g. Sixteen of these reports involved multiple drug ingestions.

Twenty-two reports indicated patients had recovered from diltiazem overdose ranging from less than 1 g to 10.8 g. There were seven reports with a fatal outcome; although the amount of diltiazem ingested was unknown, multiple drug ingestions were confirmed in six of the seven reports.

Events observed following diltiazem overdose included bradycardia, hypotension, heart block, and cardiac failure. Most reports of overdose described some supportive medical measure and/or drug treatment. Bradycardia frequently responded favorably to atropine as did heart block, although cardiac pacing was also frequently utilized to treat heart block. Fluids and vasopressors were used to maintain blood pressure and in cases of cardiac failure, inotropic agents were administered. In addition, some patients received treatment with ventilatory support, gastric lavage, activated charcoal, and/or intravenous calcium.

In the event of overdose or exaggerated response, institute appropriate supportive measures and gastrointestinal decontamination. Diltiazem does not appear to be removed by peritoneal or hemodialysis. Limited data suggest that plasmapheresis or charcoal hemoperfusion may hasten diltiazem elimination following overdose. Based on the known pharmacological effects of diltiazem and/or reported clinical experiences, the following measures may be considered:

Bradycardia: Administer atropine (0.60 to 1.0 mg). If there is no response to vagal blockage, administer isoproterenol cautiously.

High-degree AV Block: Treat as for bradycardia above. Fixed high-degree AV block should be treated with cardiac pacing.

Cardiac Failure: Administer inotropic agents (isoproterenol, dopamine, or dobutamine) and diuretics.

Hypotension: Use vasopressors (e.g., dopamine or norepinephrine).

Actual treatment and dosage should depend on the severity of the clinical situation and the judgment and experience of the treating physician.

11 DESCRIPTION

CARDIZEM® LA (diltiazem hydrochloride) is a nondihydropyridine calcium channel blocker (slow channel blocker or calcium antagonist). Chemically, diltiazem hydrochloride is 1,5-benzothiazepin-4(5H)-one, 3-(acetyloxy)-5-[2-(dimethylamino)ethyl]-2, 3-dihydro-2-(4-methoxyphenyl)-, monohydrochloride, (+)-cis-. The structural formula is:

Diltiazem hydrochloride is a white to off-white crystalline powder with a bitter taste. It is soluble in water, methanol and chloroform. It has a molecular weight of 450.98. CARDIZEM LA is formulated as a once-a-day extended-release tablet for oral administration containing 120 mg, 180 mg, 240 mg, 300 mg, 360 mg or 420 mg of diltiazem hydrochloride.

Tablets also contain: carnauba wax, colloidal silicon dioxide, croscarmellose sodium, ethyl acrylate and methyl methacrylate copolymer dispersion, hydrogenated vegetable oil, hypromellose, magnesium stearate, microcrystalline cellulose, paraffin wax, polydextrose, polyethylene glycol, polysorbate, povidone, pregelatinized starch, simethicone, sodium starch glycolate, sucrose stearate, talc, and titanium dioxide.

12 CLINICAL PHARMACOLOGY

12.1 Mechanism of Action

The therapeutic effects of diltiazem are believed to be related to its ability to inhibit the cellular influx of calcium ions during membrane depolarization of cardiac and vascular smooth muscle.

Hypertension: Diltiazem produces its antihypertensive effect primarily by relaxation of vascular smooth muscle and the resultant decrease in peripheral vascular resistance. The magnitude of blood pressure reduction is related to the degree of hypertension; thus hypertensive individuals experience an antihypertensive effect, whereas there is only a modest fall in blood pressure in normotensives.

Angina: Diltiazem has been shown to produce increases in exercise tolerance, probably due to its ability to reduce myocardial oxygen demand. This is accomplished via reductions in heart rate and systemic blood pressure at submaximal and maximal workloads. Diltiazem has been shown to be a potent dilator of coronary arteries, both epicardial and subendocardial. Spontaneous and ergonovine-induced coronary artery spasms are inhibited by diltiazem.

In animal models, diltiazem interferes with the slow inward (depolarizing) current in excitable tissue. Diltiazem causes excitation-contraction uncoupling in various myocardial. Diltiazem produces relaxation of coronary vascular smooth muscle and dilation of both large and small coronary arteries at drug levels which cause little or no negative inotropic effect. The resultant increases in coronary blood flow (epicardial and subendocardial) occur in ischemic and nonischemic models and are accompanied by dose-dependent decreases in systemic blood pressure and decreases in peripheral resistance.

12.2 Pharmacodynamics

Like other calcium channel antagonists, diltiazem decreases sinoatrial and atrioventricular conduction in isolated tissues and has a negative inotropic effect in isolated preparations. In the intact animal, prolongation of the AH interval can be seen at higher doses.

In man, diltiazem prevents spontaneous and ergonovine-provoked coronary artery spasm. It causes a decrease in peripheral vascular resistance and a modest fall in blood pressure in normotensive individuals and, in exercise tolerance studies in patients with ischemic heart disease, reduces the heart rate-blood pressure product for any given workload. Studies to date, primarily in patients with good ventricular function, have not revealed evidence of a negative inotropic effect; cardiac output, ejection fraction, and left ventricular end diastolic pressure have not been affected. Such data have no predictive value with respect to effects in patients with poor ventricular function, and increased heart failure has been reported in patients with preexisting impairment of ventricular function. There are as yet few data on the interaction of diltiazem and beta-blockers in patients with poor ventricular function. Resting heart rate is usually slightly reduced by diltiazem. Diltiazem decreases vascular resistance, increases cardiac output (by increasing stroke volume), and produces a slight decrease or no change in heart rate.

During dynamic exercise, increases in diastolic pressure are inhibited, while maximum achievable systolic pressure is usually reduced. Chronic therapy with diltiazem produces no change or an increase in plasma catecholamines. No increased activity of the renin-angiotensin-aldosterone axis has been observed. Diltiazem reduces the renal and peripheral effects of angiotensin II. Hypertensive animal models respond to diltiazem with reductions in blood pressure and increased urinary output and natriuresis without a change in urinary sodium/potassium ratio.

Intravenous diltiazem hydrochloride 20 mg prolongs AH conduction time and AV node functional and effective refractory periods by approximately 20%. In a study involving single oral doses of diltiazem hydrochloride 300 mg in six normal volunteers, the average maximum PR prolongation was 14% with no instances of greater than first-degree AV block.

Diltiazem associated prolongation of the AH interval is not more pronounced in patients with first-degree heart block. In patients with sick sinus syndrome, diltiazem significantly prolongs sinus cycle length (up to 50% in some cases).

Chronic oral administration of diltiazem hydrochloride to patients in doses of up to 540 mg/day has resulted in small increases in PR interval, and on occasion produces abnormal prolongation [see Warnings and Precautions (5.1)].

12.3 Pharmacokinetics

Diltiazem is well absorbed from the gastrointestinal tract and is subject to an extensive first-pass effect, giving an absolute bioavailability (compared to intravenous administration) of about 40%. Diltiazem undergoes extensive metabolism in which only 2% to 4% of the unchanged drug appears in the urine. Drugs that induce or inhibit hepatic microsomal enzymes may alter diltiazem disposition.

Total radioactivity measurement following short IV administration in healthy volunteers suggests the presence of other unidentified metabolites, which attain higher concentrations than those of diltiazem and are more slowly eliminated; half-life of total radioactivity is about 20 hours compared to 2 to 5 hours for diltiazem.

In vitro binding studies show diltiazem is 70% to 80% bound to plasma proteins. Competitive in vitro ligand binding studies have also shown diltiazem hydrochloride binding is not altered by therapeutic concentrations of digoxin, hydrochlorothiazide, phenylbutazone, propranolol, salicylic acid, or warfarin. The plasma elimination half-life following single or multiple drug administration is approximately 3.0 to 4.5 hours. Desacetyl diltiazem is also present in the plasma at levels of 10% to 20% of the parent drug and is 25% to 50% as potent as a coronary vasodilator as diltiazem. Minimum therapeutic plasma diltiazem concentrations appear to be in the range of 50 to 200 ng/mL. There is a departure from linearity when dose strengths are increased; the half-life is slightly increased with dose. A study that compared patients with normal hepatic function to patients with cirrhosis found an increase in half-life and a 69% increase in bioavailability in the hepatically impaired patients. A single study in nine patients with severely impaired renal function showed no difference in the pharmacokinetic profile of diltiazem compared to patients with normal renal function.

CARDIZEM LA Tablets: A single 360 mg dose of CARDIZEM LA results in detectable plasma levels within 3 to 4 hours and peak plasma levels between 11 and 18 hours; absorption occurs throughout the dosing interval. The apparent elimination half-life for CARDIZEM LA Tablets after single or multiple dosing is 6 to 9 hours. When CARDIZEM LA Tablets were coadministered with a high fat content breakfast, diltiazem peak and systemic exposures were not affected indicating that the tablet can be administered without regard to food. As the dose of CARDIZEM LA Tablets is increased from 120 to 240 mg, area-under-the-curve (AUC) increases 2.5-fold.

Drug Interactions

Impact of Diltiazem on Other Coadministered Drugs

Anesthetics: The depression of cardiac contractility, conductivity, and automaticity as well as the vascular dilation associated with anesthetics may be potentiated by calcium channel blockers. When used concomitantly, anesthetics and calcium blockers should be titrated carefully.

Benzodiazepines: Studies showed that diltiazem increased the AUC of midazolam and triazolam by 3- to 4-fold and the Cmax by 2-fold, compared to placebo. The elimination half-life of midazolam and triazolam also increased (1.5- to 2.5-fold) during coadministration with diltiazem. These pharmacokinetic effects seen during diltiazem coadministration can result in increased clinical effects (e.g., prolonged sedation) of both midazolam and triazolam.

Beta-blockers: Controlled and uncontrolled domestic studies suggest that concomitant use of diltiazem and beta-blockers is usually well tolerated, but available data are not sufficient to predict the effects of concomitant treatment in patients with left ventricular dysfunction or cardiac conduction abnormalities.

Administration of diltiazem concomitantly with propranolol in five normal volunteers resulted in increased propranolol levels in all subjects and bioavailability of propranolol was increased approximately 50%. In vitro, propranolol appears to be displaced from its binding sites by diltiazem. If combination therapy is initiated or withdrawn in conjunction with propranolol, an adjustment in the propranolol dose may be warranted [see Warnings and Precautions (5.1, 5.2)].

Buspirone: In nine healthy subjects, diltiazem significantly increased the mean buspirone AUC 5.5-fold and Cmax 4.1-fold compared to placebo. The elimination half-life and Tmax of buspirone were not significantly affected by diltiazem. Enhanced effects and increased toxicity of buspirone may be possible during concomitant administration with diltiazem. Subsequent dose adjustments may be necessary during coadministration, and should be based on clinical assessment.

Carbamazepine: Concomitant administration of diltiazem with carbamazepine has been reported to result in elevated serum levels of carbamazepine (40% to 72% increase), resulting in toxicity in some cases.

Clonidine: Sinus bradycardia resulting in hospitalization and pacemaker insertion has been reported in association with the use of clonidine concurrently with diltiazem. Monitor heart rate in patients receiving concomitant diltiazem and clonidine.

Cyclosporine: A pharmacokinetic interaction between diltiazem and cyclosporine has been observed during studies involving renal and cardiac transplant patients. In renal and cardiac transplant recipients, a reduction of cyclosporine dose ranging from 15% to 48% was necessary to maintain cyclosporine trough concentrations similar to those seen prior to the addition of diltiazem. If these agents are to be administered concurrently, cyclosporine concentrations should be monitored, especially when diltiazem therapy is initiated, adjusted, or discontinued. The effect of cyclosporine on diltiazem plasma concentrations has not been evaluated.

Digitalis: Administration of diltiazem with digoxin in 24 healthy male subjects increased plasma digoxin concentrations approximately 20%. Another investigator found no increase in digoxin levels in 12 patients with coronary artery disease. Monitor digoxin levels when initiating, adjusting, and discontinuing diltiazem therapy to avoid possible over- or under-digitalization [see Warnings and Precautions (5.1)].

Quinidine: Diltiazem increases the AUC (0→∞) of quinidine by 51%, elimination half-life by 36%, and decreases its oral clearance by 33%. Monitor for quinidine adverse effects and adjust the dose adjusted.

Statins: Diltiazem has been shown to increase significantly the AUC of some statins. The risk of myopathy and rhabdomyolysis with statins metabolized by CYP3A4 may be increased with concomitant use of diltiazem. When possible, use a non-CYP3A4-metabolized statin together with diltiazem; otherwise, dose adjustments for both diltiazem and the statin should be considered along with close monitoring for signs and symptoms of any statin-related adverse events.

In a healthy volunteer cross-over study (N=10), coadministration of a single 20 mg dose of simvastatin at the end of a 14-day regimen with 120 mg BID diltiazem SR resulted in a 5-fold increase in mean simvastatin AUC versus simvastatin alone. Subjects with increased average steady-state exposures of diltiazem showed a greater fold increase in simvastatin exposure. Computer-based simulations showed that at a daily dose of 480 mg of diltiazem, an 8- to 9-fold mean increase in simvastatin AUC can be expected. If coadministration of simvastatin with diltiazem is required, limit the daily doses of simvastatin to 10 mg and diltiazem to 240 mg.

In a 10-subject randomized, open label, 4-way cross-over study, coadministration of diltiazem (120 mg BID diltiazem SR for 2 weeks) with a single 20 mg dose of lovastatin resulted in 3- to 4-fold increase in mean lovastatin AUC and Cmax versus lovastatin alone. In the same study, there was no significant change in 20 mg single dose pravastatin AUC and Cmax during diltiazem coadministration. Diltiazem plasma levels were not significantly affected by lovastatin or pravastatin.

Impact of Other Coadministered Drugs on Diltiazem Include, but Not Limited to:

Rifampin: Coadministration of rifampin with diltiazem lowered the diltiazem plasma concentrations to undetectable levels. Coadministration of diltiazem with rifampin or any known CYP3A4 inducer should be avoided when possible, and alternative therapy considered.

Cimetidine and Ranitidine: A study in six healthy volunteers has shown a significant increase in peak diltiazem plasma levels (58%) and AUC (53%) after a 1-week course of cimetidine at 1200 mg per day and a single dose of diltiazem 60 mg. Ranitidine produced smaller, non-significant increases. The effect may be mediated by cimetidine's known inhibition of hepatic cytochrome P450, the enzyme system responsible for the first-pass metabolism of diltiazem. Patients currently receiving diltiazem therapy should be carefully monitored for a change in pharmacological effect when initiating and discontinuing therapy with cimetidine. An adjustment in the diltiazem dose may be warranted.

13 NONCLINICAL TOXICOLOGY

13.1 Carcinogenesis, Mutagenesis, Impairment of Fertility

A 24-month study in rats at oral dosage levels of up to 100 mg/kg/day, and a 21-month study in mice at oral dosage levels of up to 30 mg/kg/day showed no evidence of carcinogenicity. There was also no mutagenic response in vitro or in vivo in mammalian cell assays or in vitro in bacteria. No evidence of impaired fertility was observed in a study performed in male and female rats at oral dosages of up to 100 mg/kg/day.

14 CLINICAL STUDIES

14.1 Hypertension

In a randomized, double-blind, parallel-group, dose-response study involving 478 patients with essential hypertension, evening doses of CARDIZEM LA 120, 240, 360, and 540 mg were compared to placebo and to 360 mg administered in the morning. The mean reductions in diastolic blood pressure by ABPM at roughly 24 hours after the morning (4 AM to 8 AM) or evening (6 PM to 10 PM) administration (i.e., the time corresponding to expected trough serum concentrations) are shown in the table below:

Mean Change in Trough Diastolic Pressure by ABPM
Evening Dosing |  |  |  | Morning Dosing
120 mg | 240 mg | 360 mg | 540 mg | 360 mg
-2.0 | -4.4 | -4.4 | -8.1 | -6.4

A second randomized, double-blind, parallel-group, dose-response study (N=258) evaluated CARDIZEM LA following morning doses of placebo or 120, 180, 300, or 540 mg. Diastolic blood pressure measured by supine office cuff sphygmomanometer at trough (7 AM to 9 AM) decreased in an apparently linear manner over the dosage range studied. Group mean changes for placebo, 120 mg, 180 mg, 300 mg and 540 mg were -2.6, -1.9, -5.4, -6.1, and -8.6 mm Hg, respectively.

Whether the time of administration impacts the clinical benefits of antihypertensive treatment is not known.

Postural hypotension is infrequently noted upon suddenly assuming an upright position. No reflex tachycardia is associated with the chronic antihypertensive effects.

14.2 Angina

The effects of CARDIZEM LA on angina were evaluated in a randomized, double-blind, parallel-group, dose-response trial of 311 patients with chronic stable angina. Evening doses of 180, 360, and 420 mg were compared to placebo and to 360 mg administered in the morning. All doses of CARDIZEM LA administered at night increased exercise tolerance when compared with placebo after 21 hours. The mean effect, placebo-subtracted, was 20 to 28 seconds for all three doses, and no dose-response was demonstrated. CARDIZEM LA, 360 mg, given in the morning, also improved exercise tolerance when measured 25 hours later. As expected, the effect was smaller than the effects measured only 21 hours following nighttime administration. CARDIZEM LA had a larger effect to increase exercise tolerance at peak serum concentrations than at trough.

16 HOW SUPPLIED/STORAGE AND HANDLING

CARDIZEM® LA is supplied as capsule shaped, white film-coated tablets, debossed with “B” on one side and the diltiazem content (mg) on the other.

Strength | NDC # Bottles of 30 | NDC # Bottles of 90
120 mg | 0187-2045-30 | 0187-2045-90
180 mg | 0187-2046-30 | 0187-2046-90
240 mg | 0187-2047-30 | 0187-2047-90
300 mg | 0187-2048-30 | 0187-2048-90
360 mg | 0187-2049-30 | 0187-2049-90
420 mg | 0187-2050-30 | 0187-2050-90

Storage Conditions: Store at 25°C (77°F); excursions permitted to 15° to 30°C (59° to 86°F) [see USP Controlled Room Temperature].

Avoid excessive humidity and temperatures above 30°C (86°F).

Dispense in tight, light resistant container as defined in USP.

17 PATIENT COUNSELING INFORMATION

Advise patients:

- That the CARDIZEM LA tablet should be swallowed whole and not chewed or crushed.
- To consult the physician who prescribed CARDIZEM LA before taking or stopping any other medications, including over-the-counter products or nutritional supplements, such as St. John’s wort.
- To contact the physician who prescribed CARDIZEM LA or any other physician immediately if they experience possible adverse reactions, including bradycardia, arrhythmias, symptoms indicative of hypotension or heart failure, hepatic and skin reactions.
- To consult their physician if they become pregnant while taking CARDIZEM LA or plan to become pregnant.

Distributed by:
Bausch Health US, LLC
Bridgewater, NJ 08807 USA

Manufactured by:
Bausch Health Companies Inc.
Steinbach, MB R5G 1Z7, Canada

Cardizem is a registered trademark of Bausch Health Companies Inc. or its affiliates.

© 2025 Bausch Health Companies Inc. or its affiliates

9457003 20005829

PRINCIPAL DISPLAY PANEL – 120 mg Bottle Label

NDC 0187-2045-90

Rx only

CARDIZEM® LA
(Diltiazem Hydrochloride)
Extended-Release Tablets

120 mg

90 Tablets

BAUSCH Health

PRINCIPAL DISPLAY PANEL - 180 mg Bottle Label

NDC 0187-2046-90

Rx only

CARDIZEM® LA
(Diltiazem Hydrochloride)
Extended-Release Tablets

180 mg

90 Tablets

BAUSCH Health

PRINCIPAL DISPLAY PANEL - 240 mg Bottle Label

NDC 0187-2047-90

Rx only

CARDIZEM® LA
(Diltiazem Hydrochloride)
Extended-Release Tablets

240 mg

90 Tablets

BAUSCH Health

PRINCIPAL DISPLAY PANEL - 300 mg Bottle Label

NDC 0187-2048-90

Rx only

CARDIZEM® LA
(Diltiazem Hydrochloride)
Extended-Release Tablets

300 mg

90 Tablets

BAUSCH Health

PRINCIPAL DISPLAY PANEL - 360 mg Bottle Label

NDC 0187-2049-90

Rx only

CARDIZEM® LA
(Diltiazem Hydrochloride)
Extended-Release Tablets

360 mg

90 Tablets

BAUSCH Health

PRINCIPAL DISPLAY PANEL - 420 mg Bottle Label

NDC 0187-2050-90

Rx only

CARDIZEM® LA
(Diltiazem Hydrochloride)
Extended-Release Tablets

420 mg

90 Tablets

BAUSCH Health